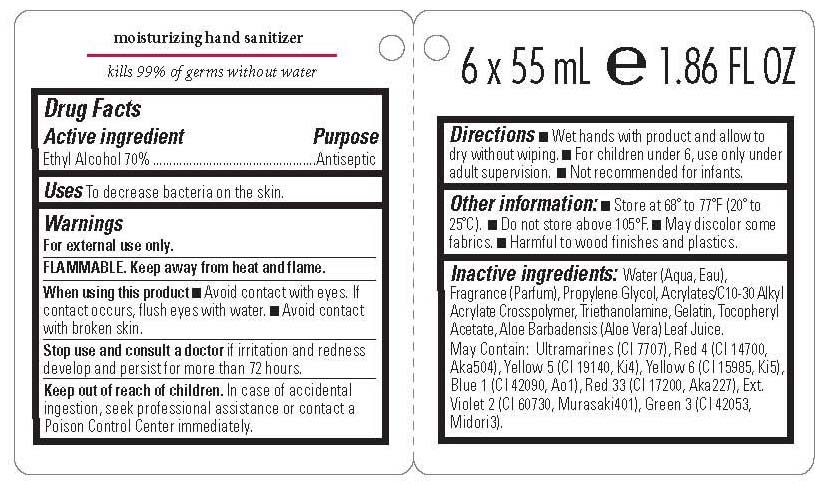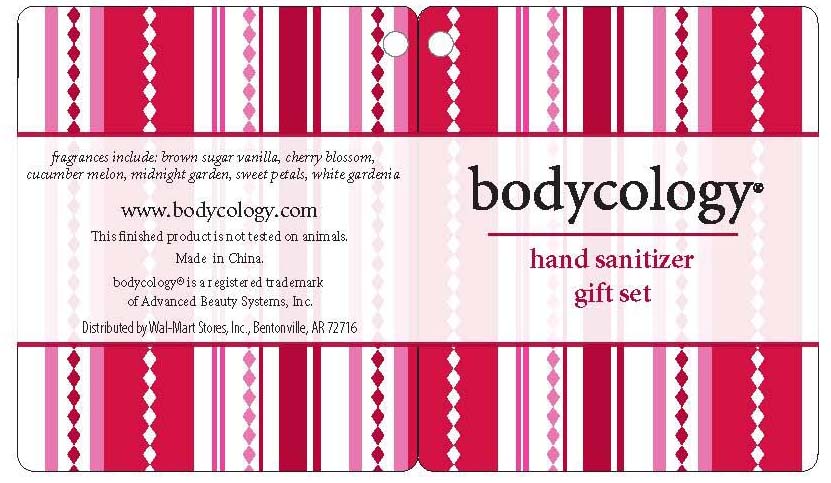 DRUG LABEL: Bodycology
NDC: 51706-400 | Form: GEL
Manufacturer: Landy International
Category: otc | Type: HUMAN OTC DRUG LABEL
Date: 20100816

ACTIVE INGREDIENTS: ALCOHOL 70 mL/100 mL

Bodycology Hand Sanitizer Gift Set Fragrances Include: brown sugar, cherry blossom, cucumber melon, midnight garden, sweet petals, white gardenia

OVERDOSAGE

Active Ingredients Purpose

Ethyl Alcohol 70% Antiseptic

Warnings:

-For external use only.

-Flammable. Keep away from heat and flame.

-Stop use and consult doctor if irritation and redness develop and persist for more than 72 hours.

PURPOSE

Uses: to decrease bacteria on the skin

Keep out of reach of children. In case of accidental ingestion, seek professional assistance or contact a Poison Control Center immediately

When using this product avoid contact with eyes. If contact occurs, flush eyes with water. Avoid contact with broken skin.

DOSAGE AND ADMINISTRATION

Directions: wet hands with product and allow to dry without whiping. For children under 6, use only under adult supervision. Not recommended for infants.

Inactive Ingredient: Water (Aqua/Eau), Fragrance (Parfum), Propylene Glycol, Acrylates/C10-30 Alkyl Acrylate Crosspolymer, Triethanolamine, Gelatin, Tocopheryl Acetate, Aloe Barbadensis (Aloe Vera). May Contain: Ultramarines (CI 77007), Red 4 (CI 14700), Yellow 5 (CI 19140), Yellow 6 (CI 15985), Blue 1 (CI 42090), Red 33 (CI 17200), Ext. Violet (CI 60730, Green 3 (CI 42053)

PACKAGE LABEL

Bodycology
Hand Sanitizer Gift Set (Fragrances Include: brown sugar vanilla, cherry blossom, cucumber melon, midnight garden, sweet petals, white gardenia
6 x 55 ml 1.86 oz